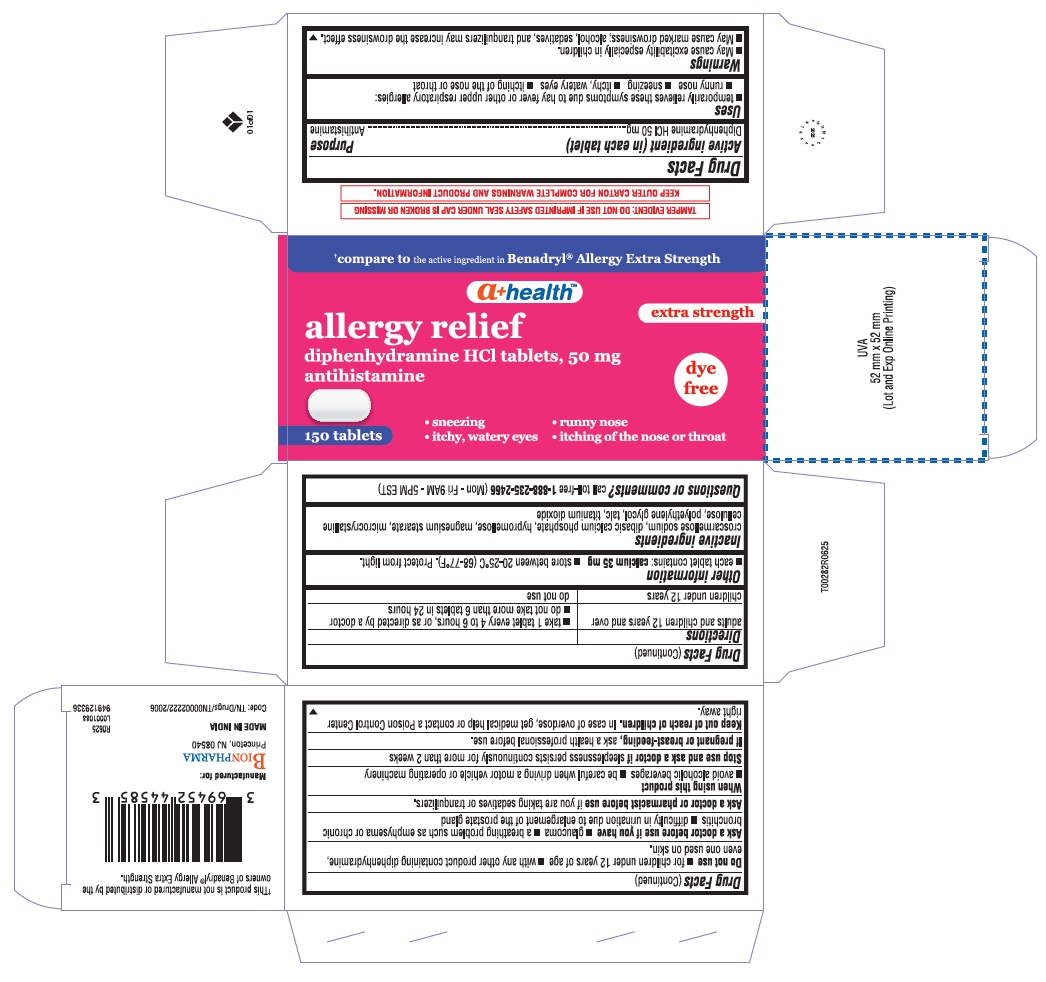 DRUG LABEL: Allergy Relief
NDC: 69452-445 | Form: TABLET
Manufacturer: BIONPHARMA INC.
Category: otc | Type: HUMAN OTC DRUG LABEL
Date: 20260112

ACTIVE INGREDIENTS: DIPHENHYDRAMINE HYDROCHLORIDE 50 mg/1 1
INACTIVE INGREDIENTS: TALC; TITANIUM DIOXIDE; CROSCARMELLOSE SODIUM; ANHYDROUS DIBASIC CALCIUM PHOSPHATE; HYPROMELLOSE, UNSPECIFIED; MAGNESIUM STEARATE; MICROCRYSTALLINE CELLULOSE; POLYETHYLENE GLYCOL, UNSPECIFIED

Diphenhydramine HCl 50 mg tablet, A+ Health, allergy relief dye free

Active ingredient (in each capsule)

Diphenhydramine HCl 50 mg

Purpose

Antihistamine

Uses

■ temporarily relieves these symptoms due to hay fever or the other upper respiratory allergies:
■ runny nose ■ sneezing ■ itchy, watery eyes ■ itching of the nose or throat

Warnings

■ May cause excitability especially in children.

■ May cause drowsiness; alcohol, sedatives, and tranquilizers may increase the drowsiness effect.

Do not use

■ for children under 12 years of age ■ with any other product containing diphenhydramine, even one used on skin.

Ask a doctor before use if you have

■ glaucoma ■ a breathing problem such as emphysema or chronic bronchitis
■ difficulty in urination due to enlargement of the prostate gland

Ask a doctor or pharmacist before use

if you are taking sedatives or tranquilizers.

When using this product

■ avoid alcoholic drinks ■ be careful when driving a motor vehicle or operating machinery

Stop use and ask a doctor if

sleeplessness persisits continuously for more than 2 weeks

If pregnant or breast- feeding,

ask a health professional before use.

Keep out of reach of children.

In case of overdose, get medical help or contact a Poison Control Centre right away.

Directions

adults and children 12 years and over | ■ take 1 tablet every 4 to 6 hours, or as directed by the doctor; ■ do not take more than 6 tablets in 24 hours
children under 12 years | do not use

Other information

■ each tablet contains: calcium 35 mg■ store between 20-25°C (68-77°F). Protect from light.

■ do not use if blister unit is torn or broken

Inactive ingredients

croscarmellose sodium, dibasic calcium phosphate, hypromellose, magnesium stearate, microcrystalline cellulose, polyethylene glycol, talc, titanium dioxide

Questions or comments?

call toll-free 1-888-235-2466(Mon - Fri 9AM - 5PM EST)

†This product is not manufactured or distributed by the owners of Benadryl® Allergy Extra Strength

THIS PRODUCT IS PACKAGED IN A CHILD-RESISTANT AND

TAMPER-EVIDENT PACKAGE. USE ONLY IF BLISTERS ARE INTACT.

KEEP OUTER CARTON FOR COMPLETE

WARNINGS AND PRODUCT INFORMATION.

Manufactured for:

BIONPHARMA INC.
Princeton, NJ 08540

MADE IN INDIA

949129336

Code: TN/Drugs/TN00002222/2006

L0001088

R0625

150''s count

†Compare tothe active ingredient in Benadryl® Allergy Extra Strength

a+ healthTM

extra strength
allergy relief

diphenhydramine HCl tablets,50 mg

antihistamine

dye

free

150 tablets

• sneezing • runny nose
• itchy, watery eyes • itching of the nose or throat